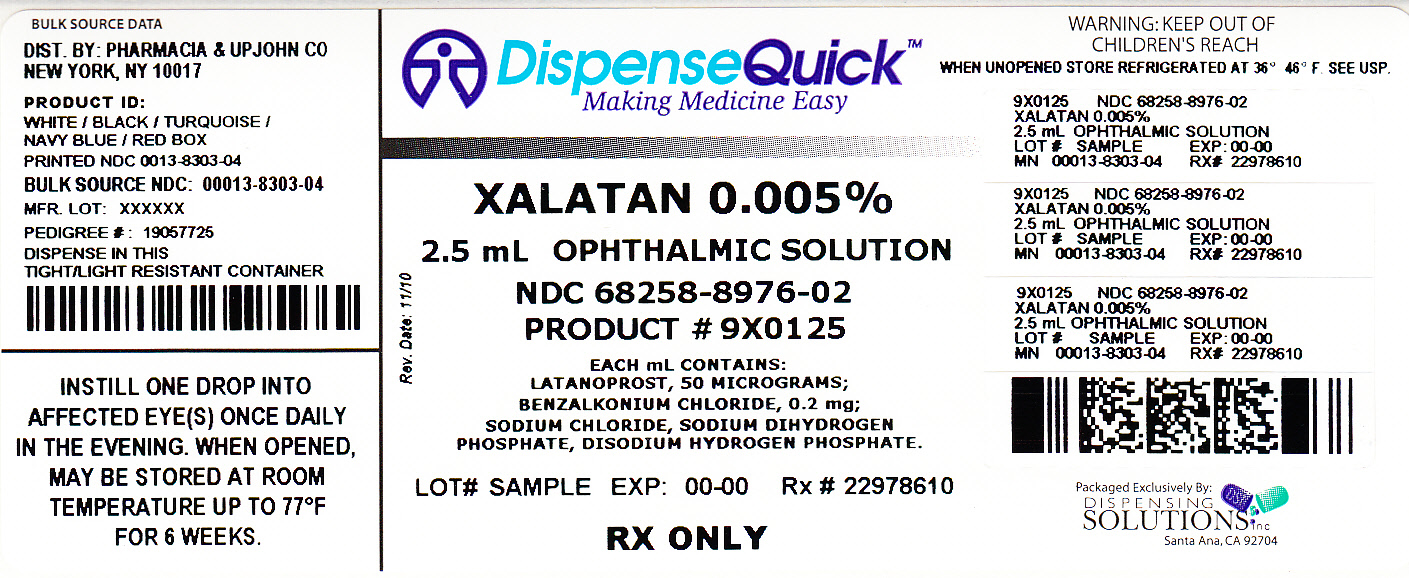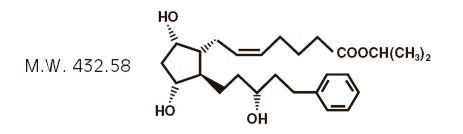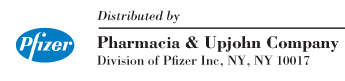 DRUG LABEL: Xalatan
NDC: 68258-8976 | Form: SOLUTION
Manufacturer: Dispensing Solutions, Inc.
Category: prescription | Type: HUMAN PRESCRIPTION DRUG LABEL
Date: 20111006

ACTIVE INGREDIENTS: latanoprost 50 ug/1 mL
INACTIVE INGREDIENTS: Benzalkonium chloride; sodium chloride; sodium phosphate, dibasic anhydrous; water

Xalatan®
latanoprost ophthalmic solution
0.005% (50 µg/mL)

DESCRIPTION

Latanoprost is a prostaglandin F2α analogue. Its chemical name is isopropyl-(Z)-7[(1R,2R,3R,5S)3,5-dihydroxy-2-[(3R)-3-hydroxy-5-phenylpentyl]cyclopentyl]-5-heptenoate. Its molecular formula is C26H40O5 and its chemical structure is:

Latanoprost is a colorless to slightly yellow oil that is very soluble in acetonitrile and freely soluble in acetone, ethanol, ethyl acetate, isopropanol, methanol and octanol. It is practically insoluble in water.

XALATAN Sterile Ophthalmic Solution (latanoprost ophthalmic solution) is supplied as a sterile, isotonic, buffered aqueous solution of latanoprost with a pH of approximately 6.7 and an osmolality of approximately 267 mOsmol/kg. Each mL of XALATAN contains 50 micrograms of latanoprost. Benzalkonium chloride, 0.02% is added as a preservative. The inactive ingredients are: sodium chloride, sodium dihydrogen phosphate monohydrate, disodium hydrogen phosphate anhydrous and water for injection. One drop contains approximately 1.5 µg of latanoprost.

CLINICAL PHARMACOLOGY

Mechanism of Action

Latanoprost is a prostanoid selective FP receptor agonist that is believed to reduce the intraocular pressure (IOP) by increasing the outflow of aqueous humor. Studies in animals and man suggest that the main mechanism of action is increased uveoscleral outflow. Elevated IOP represents a major risk factor for glaucomatous field loss. The higher the level of IOP, the greater the likelihood of optic nerve damage and visual field loss.

Pharmacokinetics/Pharmacodynamics

Absorption

Latanoprost is absorbed through the cornea where the isopropyl ester prodrug is hydrolyzed to the acid form to become biologically active. Studies in man indicate that the peak concentration in the aqueous humor is reached about two hours after topical administration.

Distribution

The distribution volume in humans is 0.16 ± 0.02 L/kg. The acid of latanoprost can be measured in aqueous humor during the first 4 hours, and in plasma only during the first hour after local administration.

Metabolism

Latanoprost, an isopropyl ester prodrug, is hydrolyzed by esterases in the cornea to the biologically active acid. The active acid of latanoprost reaching the systemic circulation is primarily metabolized by the liver to the 1,2-dinor and 1,2,3,4-tetranor metabolites via fatty acid β-oxidation.

Excretion

The elimination of the acid of latanoprost from human plasma is rapid (t1/2 =17 min) after both intravenous and topical administration. Systemic clearance is approximately 7 mL/min/kg. Following hepatic β-oxidation, the metabolites are mainly eliminated via the kidneys. Approximately 88% and 98% of the administered dose is recovered in the urine after topical and intravenous dosing, respectively.

Animal Studies

In monkeys, latanoprost has been shown to induce increased pigmentation of the iris. The mechanism of increased pigmentation seems to be stimulation of melanin production in melanocytes of the iris, with no proliferative changes observed. The change in iris color may be permanent.

Ocular administration of latanoprost at a dose of 6 µg/eye/day (4 times the daily human dose) to cynomolgus monkeys has also been shown to induce increased palpebral fissure. This effect was reversible upon discontinuation of the drug.

INDICATIONS AND USAGE

XALATAN Sterile Ophthalmic Solution is indicated for the reduction of elevated intraocular pressure in patients with open-angle glaucoma or ocular hypertension.

CLINICAL STUDIES

Patients with mean baseline intraocular pressure of 24 – 25 mmHg who were treated for 6 months in multi-center, randomized, controlled trials demonstrated 6 –8 mmHg reductions in intraocular pressure. This IOP reduction with XALATAN Sterile Ophthalmic Solution 0.005% dosed once daily was equivalent to the effect of timolol 0.5% dosed twice daily.

A 3-year open-label, prospective safety study with a 2-year extension phase was conducted to evaluate the progression of increased iris pigmentation with continuous use of XALATAN once-daily as adjunctive therapy in 519 patients with open-angle glaucoma. The analysis was based on observed-cases population of the 380 patients who continued in the extension phase.

Results showed that the onset of noticeable increased iris pigmentation occurred within the first year of treatment for the majority of the patients who developed noticeable increased iris pigmentation. Patients continued to show signs of increasing iris pigmentation throughout the five years of the study. Observation of increased iris pigmentation did not affect the incidence, nature or severity of adverse events (other than increased iris pigmentation) recorded in the study. IOP reduction was similar regardless of the development of increased iris pigmentation during the study.

CONTRAINDICATIONS

Known hypersensitivity to latanoprost, benzalkonium chloride or any other ingredients in this product.

WARNINGS

XALATAN Sterile Ophthalmic Solution has been reported to cause changes to pigmented tissues. The most frequently reported changes have been increased pigmentation of the iris, periorbital tissue (eyelid) and eyelashes, and growth of eyelashes. Pigmentation is expected to increase as long as XALATAN is administered. After discontinuation of XALATAN, pigmentation of the iris is likely to be permanent while pigmentation of the periorbital tissue and eyelash changes have been reported to be reversible in some patients. Patients who receive treatment should be informed of the possibility of increased pigmentation. The effects of increased pigmentation beyond 5 years are not known.

PRECAUTIONS

General

XALATAN Sterile Ophthalmic Solution may gradually increase the pigmentation of the iris. The eye color change is due to increased melanin content in the stromal melanocytes of the iris rather than to an increase in the number of melanocytes. This change may not be noticeable for several months to years (see WARNINGS). Typically, the brown pigmentation around the pupil spreads concentrically towards the periphery of the iris and the entire iris or parts of the iris become more brownish. Neither nevi nor freckles of the iris appear to be affected by treatment. While treatment with XALATAN can be continued in patients who develop noticeably increased iris pigmentation, these patients should be examined regularly.

During clinical trials, the increase in brown iris pigment has not been shown to progress further upon discontinuation of treatment, but the resultant color change may be permanent.

Eyelid skin darkening, which may be reversible, has been reported in association with the use of XALATAN (see WARNINGS).

XALATAN may gradually change eyelashes and vellus hair in the treated eye; these changes include increased length, thickness, pigmentation, the number of lashes or hairs, and misdirected growth of eyelashes. Eyelash changes are usually reversible upon discontinuation of treatment.

XALATAN should be used with caution in patients with a history of intraocular inflammation (iritis/uveitis) and should generally not be used in patients with active intraocular inflammation.

Macular edema, including cystoid macular edema, has been reported during treatment with XALATAN. These reports have mainly occurred in aphakic patients, in pseudophakic patients with a torn posterior lens capsule, or in patients with known risk factors for macular edema. XALATAN should be used with caution in patients who do not have an intact posterior capsule or who have known risk factors for macular edema.

There is limited experience with XALATAN in the treatment of angle closure, inflammatory or neovascular glaucoma.

There have been reports of bacterial keratitis associated with the use of multiple-dose containers of topical ophthalmic products. These containers had been inadvertently contaminated by patients who, in most cases, had a concurrent corneal disease or a disruption of the ocular epithelial surface (see PRECAUTIONS, Information for Patients).

Contact lenses should be removed prior to the administration of XALATAN, and may be reinserted 15 minutes after administration (see PRECAUTIONS, Information for Patients).

Information for Patients

(see WARNINGS and PRECAUTIONS)

Patients should be advised about the potential for increased brown pigmentation of the iris, which may be permanent. Patients should also be informed about the possibility of eyelid skin darkening, which may be reversible after discontinuation of XALATAN.

Patients should also be informed of the possibility of eyelash and vellus hair changes in the treated eye during treatment with XALATAN. These changes may result in a disparity between eyes in length, thickness, pigmentation, number of eyelashes or vellus hairs, and/or direction of eyelash growth. Eyelash changes are usually reversible upon discontinuation of treatment.

Patients should be instructed to avoid allowing the tip of the dispensing container to contact the eye or surrounding structures because this could cause the tip to become contaminated by common bacteria known to cause ocular infections. Serious damage to the eye and subsequent loss of vision may result from using contaminated solutions.

Patients also should be advised that if they develop an intercurrent ocular condition (e.g., trauma, or infection) or have ocular surgery, they should immediately seek their physician's advice concerning the continued use of the multiple-dose container.

Patients should be advised that if they develop any ocular reactions, particularly conjunctivitis and lid reactions, they should immediately seek their physician's advice.

Patients should also be advised that XALATAN contains benzalkonium chloride, which may be absorbed by contact lenses. Contact lenses should be removed prior to administration of the solution. Lenses may be reinserted 15 minutes following administration of XALATAN.

If more than one topical ophthalmic drug is being used, the drugs should be administered at least five (5) minutes apart.

Drug Interactions

In vitro studies have shown that precipitation occurs when eye drops containing thimerosal are mixed with XALATAN. If such drugs are used they should be administered at least five (5) minutes apart.

Carcinogenesis, Mutagenesis, Impairment of Fertility

Latanoprost was not mutagenic in bacteria, in mouse lymphoma or in mouse micronucleus tests.

Chromosome aberrations were observed in vitro with human lymphocytes.

Latanoprost was not carcinogenic in either mice or rats when administered by oral gavage at doses of up to 170 µg/kg/day (approximately 2,800 times the recommended maximum human dose) for up to 20 and 24 months, respectively.

Additional in vitro and in vivo studies on unscheduled DNA synthesis in rats were negative. Latanoprost has not been found to have any effect on male or female fertility in animal studies.

Pregnancy

Teratogenic Effects

Pregnancy Category C

Reproduction studies have been performed in rats and rabbits. In rabbits an incidence of 4 of 16 dams had no viable fetuses at a dose that was approximately 80 times the maximum human dose, and the highest nonembryocidal dose in rabbits was approximately 15 times the maximum human dose. There are no adequate and well-controlled studies in pregnant women. XALATAN should be used during pregnancy only if the potential benefit justifies the potential risk to the fetus.

Nursing Mothers

It is not known whether this drug or its metabolites are excreted in human milk. Because many drugs are excreted in human milk, caution should be exercised when XALATAN is administered to a nursing woman.

Pediatric Use

Safety and effectiveness in pediatric patients have not been established.

Geriatric Use

No overall differences in safety or effectiveness have been observed between elderly and younger patients.

ADVERSE REACTIONS

Adverse events referred to in other sections of this insert

Eyelash changes (increased length, thickness, pigmentation, and number of lashes); eyelid skin darkening; intraocular inflammation (iritis/uveitis); iris pigmentation changes; and macular edema, including cystoid macular edema (see WARNINGS and PRECAUTIONS).

Controlled Clinical Trials

The ocular adverse events and ocular signs and symptoms reported in 5 to 15% of the patients on XALATAN Sterile Ophthalmic Solution in the three 6-month, multi-center, double-masked, active-controlled trials were blurred vision, burning and stinging, conjunctival hyperemia, foreign body sensation, itching, increased pigmentation of the iris, and punctate epithelial keratopathy.

Local conjunctival hyperemia was observed; however, less than 1% of the patients treated with XALATAN required discontinuation of therapy because of intolerance to conjunctival hyperemia.

In addition to the above listed ocular events/signs and symptoms, the following were reported in 1 to 4% of the patients: dry eye, excessive tearing, eye pain, lid crusting, lid discomfort/pain, lid edema, lid erythema, and photophobia.

The following events were reported in less than 1% of the patients: conjunctivitis, diplopia and discharge from the eye.

During clinical studies, there were extremely rare reports of the following: retinal artery embolus, retinal detachment, and vitreous hemorrhage from diabetic retinopathy.

The most common systemic adverse events seen with XALATAN were upper respiratory tract infection/cold/flu, which occurred at a rate of approximately 4%. Chest pain/angina pectoris, muscle/joint/back pain, and rash/allergic skin reaction each occurred at a rate of 1 to 2%.

Clinical Practice

The following events have been identified during postmarketing use of XALATAN in clinical practice. Because they are reported voluntarily from a population of unknown size, estimates of frequency cannot be made. The events, which have been chosen for inclusion due to either their seriousness, frequency of reporting, possible causal connection to XALATAN, or a combination of these factors, include: asthma and exacerbation of asthma; corneal edema and erosions; dyspnea; eyelash and vellus hair changes (increased length, thickness, pigmentation, and number); eyelid skin darkening; herpes keratitis; intraocular inflammation (iritis/uveitis); keratitis; macular edema, including cystoid macular edema; misdirected eyelashes sometimes resulting in eye irritation; dizziness, headache, and toxic epidermal necrolysis.

OVERDOSAGE

Apart from ocular irritation and conjunctival or episcleral hyperemia, the ocular effects of latanoprost administered at high doses are not known. Intravenous administration of large doses of latanoprost in monkeys has been associated with transient bronchoconstriction; however, in 11 patients with bronchial asthma treated with latanoprost, bronchoconstriction was not induced. Intravenous infusion of up to 3 µg/kg in healthy volunteers produced mean plasma concentrations 200 times higher than during clinical treatment and no adverse reactions were observed. Intravenous dosages of 5.5 to 10 µg/kg caused abdominal pain, dizziness, fatigue, hot flushes, nausea and sweating.

If overdosage with XALATAN Sterile Ophthalmic Solution occurs, treatment should be symptomatic.

DOSAGE AND ADMINISTRATION

The recommended dosage is one drop (1.5 µg) in the affected eye(s) once daily in the evening. If one dose is missed, treatment should continue with the next dose as normal.

The dosage of XALATAN Sterile Ophthalmic Solution should not exceed once daily; the combined use of two or more prostaglandins, or prostaglandin analogs including XALATAN Sterile Ophthalmic Solution is not recommended. It has been shown that administration of these prostaglandin drug products more than once daily may decrease the intraocular pressure lowering effect or cause paradoxical elevations in IOP.

Reduction of the intraocular pressure starts approximately 3 to 4 hours after administration and the maximum effect is reached after 8 to 12 hours.

XALATAN may be used concomitantly with other topical ophthalmic drug products to lower intraocular pressure. If more than one topical ophthalmic drug is being used, the drugs should be administered at least five (5) minutes apart.

HOW SUPPLIED

XALATAN Sterile Ophthalmic Solution is a clear, isotonic, buffered, preserved colorless solution of latanoprost 0.005% (50 µg/mL). It is supplied as a 2.5 mL solution in a 5 mL clear low density polyethylene bottle with a clear low density polyethylene dropper tip, a turquoise high density polyethylene screw cap, and a tamper-evident clear low density polyethylene overcap.

2.5 mL fill, 0.005% (50 µg/mL)

Package of 1 bottle NDC 0013-8303-04

Storage

Protect from light. Store unopened bottle(s) under refrigeration at 2° to 8°C (36° to 46°F). During shipment to the patient, the bottle may be maintained at temperatures up to 40°C (104°F) for a period not exceeding 8 days. Once a bottle is opened for use, it may be stored at room temperature up to 25°C (77°F) for 6 weeks.

Rx only

Manufactured By:
Catalent Pharma Solutions
Woodstock, IL 60098, USA

Pfizer Manufacturing Belgium NV
Puurs, Belgium

LAB-0135-9.0
May 2011

PRINCIPAL DISPLAY PANEL - 2.5 mL Sample Bottle Carton

NDC 68258-8976-02

Rx only

Xalatan®
latanoprost ophthalmic solution

One 2.5 mL bottle
Sterile

0.005%
(125 µg/2.5 mL)